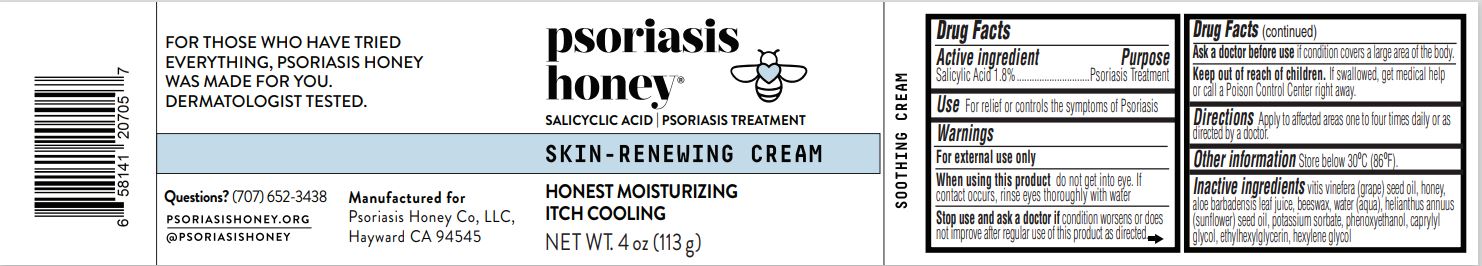 DRUG LABEL: Skin Renewing Cream
NDC: 62742-4227 | Form: CREAM
Manufacturer: Allure Labs
Category: otc | Type: HUMAN OTC DRUG LABEL
Date: 20241209

ACTIVE INGREDIENTS: SALICYLIC ACID 1.8 g/100 g
INACTIVE INGREDIENTS: HONEY; YELLOW WAX; HEXYLENE GLYCOL; CAPRYLYL GLYCOL; WATER; SUNFLOWER OIL; POTASSIUM SORBATE; ETHYLHEXYLGLYCERIN; ALOE VERA LEAF; PHENOXYETHANOL; VITIS VINIFERA SEED

Drug Facts

Active ingredient

Salicylic Acid 1.8%

Purpose

Psoriasis Treatment

INDICATIONS AND USAGE

Use For relief or controls the symptoms of Psoriasis

Warnings

For external use only

Do not use if you have a very sensitive skin or sensitive to salicylic acid.

When using this product do not get into eye. If contact occurs, rinse eyes thoroughly with water

Stop use and ask a doctor if condition worsens or does not improve after regular use of this product as directed,

Keep out of reach of children. If swallowed, get medical help or call a Poison Control Center right away

DOSAGE AND ADMINISTRATION

Directions apply to affected areas one to four times daily or as directed by a doctor

Other information Store below 30°C (86°F).

Inactive ingredients

Vitis vinefera (grape) seed oil, honey, aloe barbadensis leaf juice, beeswax, water (aqua), helianthus annuus (sunflower) seed oil, potassium sorbate, phenoxyethanol, caprylyl glycol, ethylhexylglycerin, hexylene glycol